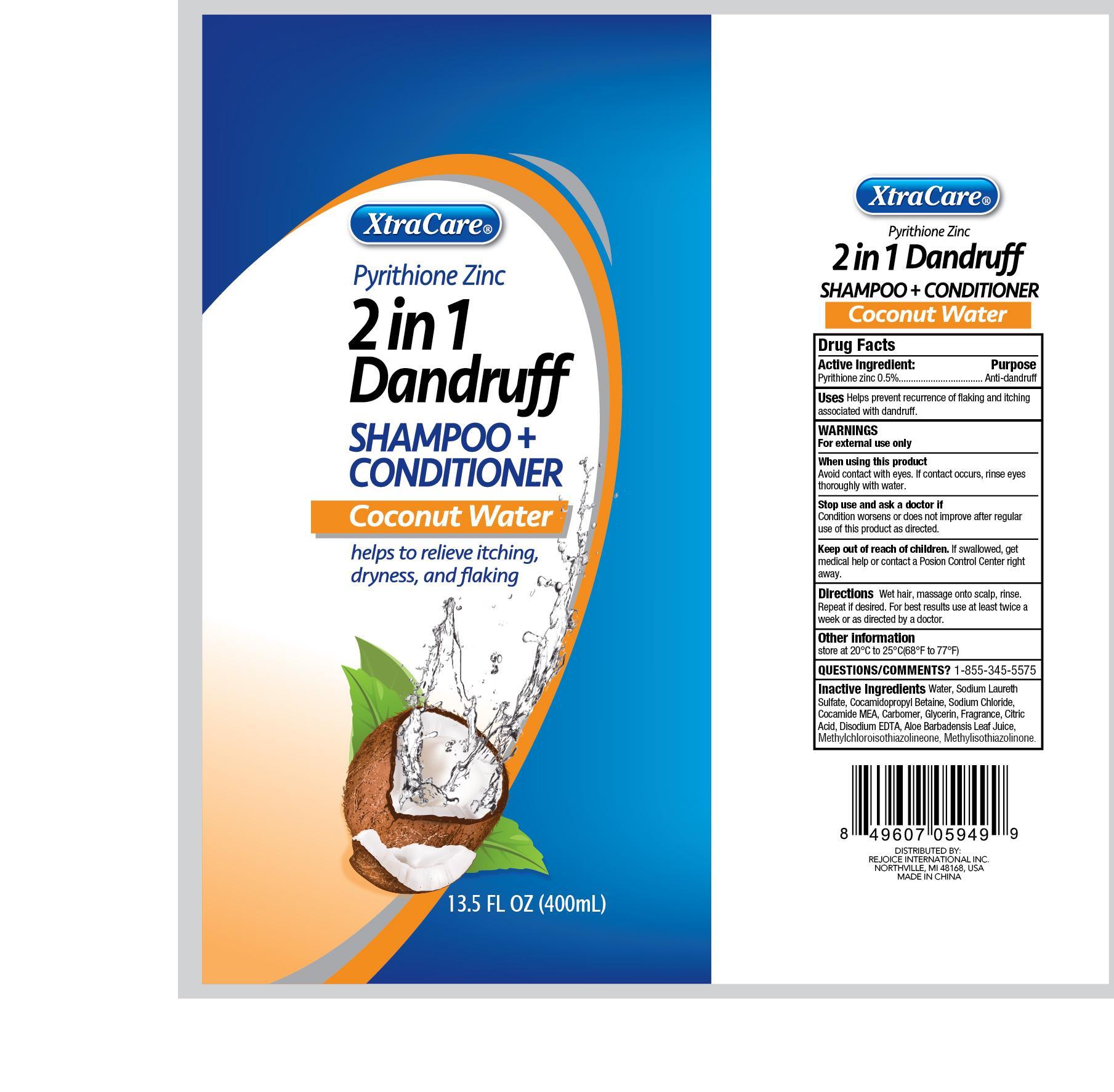 DRUG LABEL: XtraCare 2 in 1 Hair Cleanse and Condition
NDC: 58503-064 | Form: SHAMPOO
Manufacturer: China Ningbo Shangge Cosmetic Technology Corp.
Category: otc | Type: HUMAN OTC DRUG LABEL
Date: 20190913

ACTIVE INGREDIENTS: PYRITHIONE ZINC 2 g/100 g
INACTIVE INGREDIENTS: WATER; SODIUM LAURETH SULFATE; COCAMIDOPROPYL BETAINE; SODIUM CHLORIDE; COCO MONOETHANOLAMIDE; CARBOMER COPOLYMER TYPE A (ALLYL PENTAERYTHRITOL CROSSLINKED); GLYCERIN; CITRIC ACID MONOHYDRATE; EDETATE DISODIUM; ALOE VERA LEAF; METHYLCHLOROISOTHIAZOLINONE; METHYLISOTHIAZOLINONE

XtraCare 2 in 1 Hair Cleanse and Condition

Active Ingredient Purpose

Pyrithione Zinc 0.5% .......................... Anti-dandruff

Uses

Helps prevent recurrence of flaking and itching associated with dandruff.

Keep out of reach of children. If swallowed, get medical help or contact a Poison Control Center right away.

INDICATIONS AND USAGE

XtraCare Pyrithione Zinc

2 in 1 Dandruff

Shampoo + Conditioner

Coconut Water

helps to relieve itching, dryness, and flaking

Warnings

For external use only

When using this product

Avoid contact wiht eyes. If contact occurs, rinse eyes thoroughly with water.

Stop use and ask a doctor if

Condition worsens or does not improve after regular use of this product as directed.

Directions

Wet hair, massage onto scalp, rinse. Repeat if desired. For best results use at least twice a week or as directed by a doctor.

Inactive Ingredients

water, sodium laureth sulfate, cocamidopropyl betaine, sodium chloride, cocamide MEA, carbomer, glycerin, fragrance, citric acid, disodium EDTA, aloe barbadensis leaf juice, methylchloroisothiazolinone, methylisothiazolinone.

Other Information

Store at 20C to 25C (68F to 77F)

Questions/Comments? 1-855-345-5575

DISTRIBUTED BY:

REJOICE INTERNATIONAL INC.

NORTHVILLE, MI 48168, USA

MADE IN CHINA